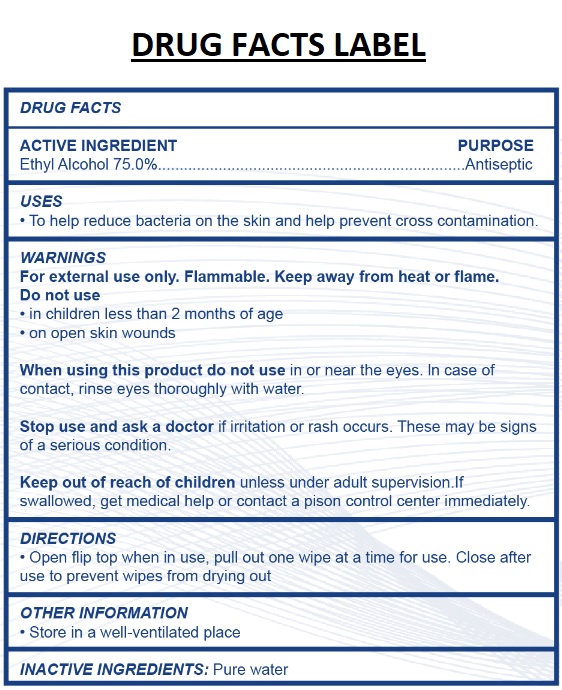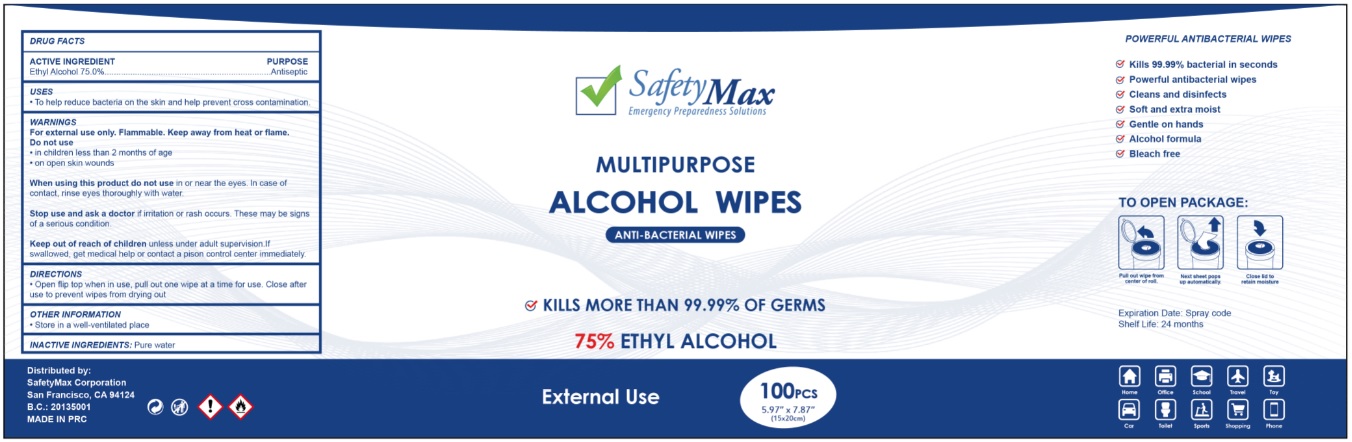 DRUG LABEL: SafetyMax ALCOHOL WIPES
NDC: 78503-200 | Form: CLOTH
Manufacturer: Safetymax Corporation
Category: otc | Type: HUMAN OTC DRUG LABEL
Date: 20200827

ACTIVE INGREDIENTS: ALCOHOL 75 mL/100 mL
INACTIVE INGREDIENTS: WATER

SafetyMax MULTIPURPOSE ALCOHOL WIPES

ACTIVE INGREDIENT

Ethyl Alcohol 75.0%

PURPOSE

Antiseptic

USES

• To help reduce bacteria on the skin and help prevent cross contamination.

WARNINGS

For external use only. Flammable. Keep away from heat or flame.

Do not use

• in children less than 2 months of age

• on open skin wounds

When using this product do not use in or near the eyes. In case of contact, rinse eyes thoroughly with water.

Stop use and ask a doctor if irritation or rash occurs. These may be signs of a serious condition.

Keep out of reach of children unless under adult supervision. If swallowed, get medical help or contact a poison control center immediately.

DIRECTIONS

• Open flip top when in use, pull out one wipe at a time for use. Close after use to prevent wipes from drying out

OTHER INFORMATION

• Store in a well-ventilated place

INACTIVE INGREDIENTS:

Pure water

Emergency Preparedness Solutions

ANTI-BACTERIAL WIPES

KILLS MORE THAN 99.99% OF GERMS

75% ETHYL ALCOHOL

External Use

Distributed by:

SafetyMax Corporation

San Francisco, CA 94124

B.C.: 20135001

MADE IN PRC

POWERFUL ANTIBACTERIAL WIPES

• Kills 99.99% bacterial in seconds

• Powerful antibacterial wipes

• Cleans and disinfects

• Soft and extra moist

• Gentle on hands

• Alcohol formula

• Bleach free

TO OPEN PACKAGE:

Pull out wipe from center of roll.

Next sheet pops up automatically.

Close lid to retain moisture

Expiration Date: Spray code

Shelf Life: 24 months

Home

Office

School

Travel

Toy

Car

Toilet

Sports

Shopping

Phone